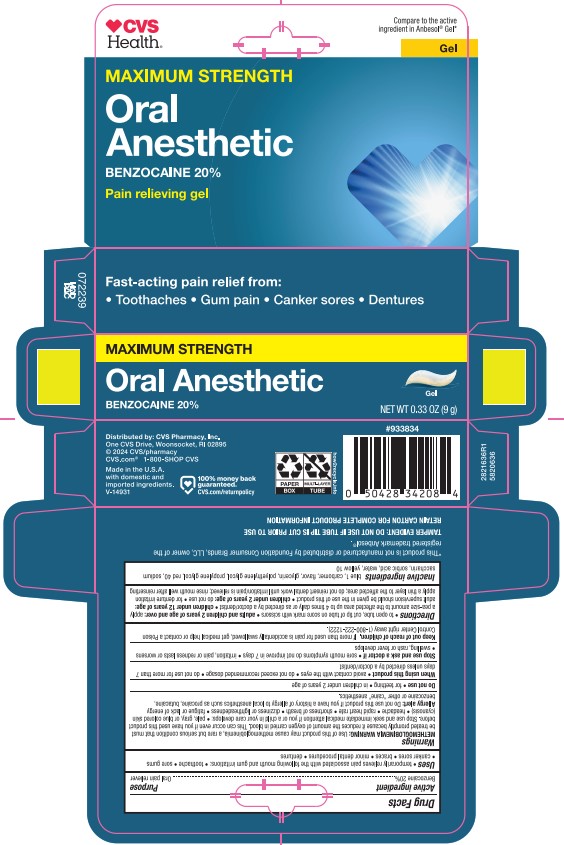 DRUG LABEL: CVS Pharmacy
NDC: 59779-582 | Form: GEL, DENTIFRICE
Manufacturer: CVS Pharmacy
Category: otc | Type: HUMAN OTC DRUG LABEL
Date: 20251113

ACTIVE INGREDIENTS: BENZOCAINE 20 g/100 g
INACTIVE INGREDIENTS: POLYETHYLENE GLYCOL 400; PROPYLENE GLYCOL; SACCHARIN SODIUM; SORBIC ACID; GLYCERIN; FD&C RED NO. 40; D&C YELLOW NO. 10; FD&C BLUE NO. 1; WATER

5820636 CVS Oral Anesthetic Gel (8015316)

Active ingredient

Benzocaine 20%

Use

temporarily relieves pain associated with mouth and gum irritations, toothache, sore gums, canker sores, braces, minor dental procedures, dentures

Purpose

Oral pain reliever

Directions

- to open tube, cut tip of tube on score mark with scissors
- adults and children 2 years of age and over: apply a pea-size amount to the affected area up to 4 times daily or as directed by a dentist/doctor.
- children under 12 years of age: adult supervision should be given in the use of this product.
- children under 2 years of age: do not use
- for denture irritation apply a thin layer to the affected area; do not reinsert dental work intil irritation/pain is relieved; rinse mouth well after reinserting

Inactive ingredients

Blue 1, Carbomer, Flavor, Glycerin, Polyethylene Glycol, Propylene Glycol, Red 40, Sodium Saccharin, Sorbic Acid, Water, Yellow 10

WARNINGS

Methemoglobinemia Warning: USe of this product may cause methemoglobinemia, a rare but serious condition that must be treated promptly because it reduces the amount of oxygen carried in blood. This can occur even if you have used this product before. Stop use and seek immediate medical attention if you or a child in your care develops: pale, gray, or blue colored skin (cyanosis), headache, rapid heart rate, shortness of breath, dizziness or lightheadedness, fatigue or lack of energy.

Allergy alert: Do not use this product if you have a history of allergy to local anesthetics such as procaine, butacaine, benzocaine or other "caine" anesthetics.

Do not use for teething, in children under 2 years of age

Keep out of reach of children. If more than used for pain is accidentally swallowed, get medical help or contact a Poison Control Center right away (1-800-222-1222).